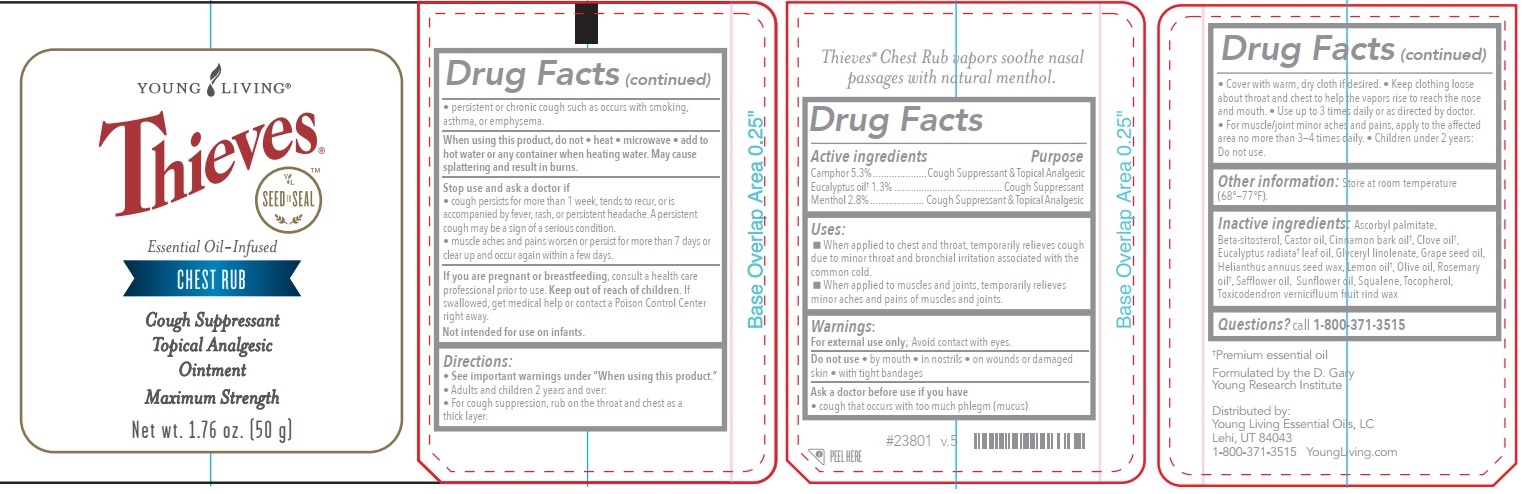 DRUG LABEL: Thieves Essential Oil-Infused Chest Rub
NDC: 70631-057 | Form: OINTMENT
Manufacturer: Young Living Essential Oils
Category: otc | Type: HUMAN OTC DRUG LABEL
Date: 20240918

ACTIVE INGREDIENTS: CAMPHOR (NATURAL) 0.053 g/1 g; MENTHOL 0.028 g/1 g; EUCALYPTUS OIL 0.013 g/1 g
INACTIVE INGREDIENTS: EUCALYPTUS RADIATA LEAF OIL; SAFFLOWER OIL; GLYCERYL LINOLENATE; TOCOPHEROL; CASTOR OIL; OLIVE OIL; ASCORBYL PALMITATE; SQUALANE; CLOVE OIL; ROSEMARY OIL; TOXICODENDRON VERNICIFLUUM FRUIT RIND WAX; CINNAMON BARK OIL; SUNFLOWER OIL; LEMON OIL; GRAPE SEED OIL; .BETA.-SITOSTEROL

Thieves™Essential Oil-Infused Chest Rub

Drug Facts

Active ingredient

Camphor 5.3%
Menthol 2.8%
Eucalyptus oil 1.3%

Purpose

Camphor .............Cough Suppressant & Topical Analgesic
Menthol ...............Cough Suppressant & Topical Analgesic
Eucalyptus oil .....Cough Suppressant

Uses

 When applied to chest and throat, temporariliy relieves cough due to minor throat and bronchial irritation associated with the common cold.
 When applied to muscles and joints, temporarily releives minor aches and pains of muscles and joints.

Uses:

Changed from "temporarily relieves stuffiness, cough, and congestion due to minor throat and bronchial congestion due to minor throat and bronchial irritation associated with the common cold" to "When applied to chest and throat, temporariliy relieves cough due to minor throat and bronchial irritation associated with the common cold. When applied to muscles and joints, temporarily releives minor aches and pains of muscles and joints."

Directions:

Changed from:

•"See warnings under " When using this product".

• Adults and children 2 years and older.
• For cough suppression • rub a thick layer on throat and chest.
• Use up to three times daily or as directed by doctor.
• Children under 2 years: Do not use.

Changed to:

• See warnings under " When using this product".

• Adults and children 2 years and older.
• For cough suppression rub on throat and chest as a thick layer.
• Cover with warm, dry cloth if desired • Keep clothing loose about throat and chest to help the vapors rise to reach the nose and mouth. • Use up to 3 times daily or as directed by doctor. • For muscle/joint minor aches and pains, apply to the affected area no more than 3—4 times daily. • Children under 2 years: Do not use.

Warnings

For external use only

- Avoid contact with eyes.
- Do not use • by mouth • in nostrils • on wounds or damaged skin • with tight bandages

Ask a doctor before use if you have
• cough that occurs with too much phlegm (mucus)

• persistent or chronic cough such as occurs with smoking, asthma, or emphysetma

Stop use and consult a doctor if:

- cough persists for more than 1 week, tends to recur, is accompanied by fever, rash or persistant headache.

A persistent cough may be a sign of a serious condition.

- muscle aches and pains worsen or persist for more than 7 days or clear up and occur again within a few

days.

When using this productdo not

- heat
- microwave
- use near open flame
- add to hot water or container where heating water

May cause splattering and result in burns.

Keep out of reach of children.

Directions

See warnings under " When using this product".

- Adults and children 2 years and older.
- For cough suppression rub on throat and chest as a thick layer.
- Cover with warm, dry cloth if desired • Keep clothing loose about throat and chest to help the vapors rise to reach the nose and mouth. • Use up to 3 times daily or as directed by doctor.
- For muscle/joint minor aches and pains, apply to the affected area no more than 3—4 times daily. • Children under 2 years: Do not use.

Other information

- Store at room temperature (68° and 77° F).

Inactive ingredients

Ascorbyl palmitate, Beta-sitosterol, Castor oil, Cinnamon bark oil †, Clove oil †, Eucalyptus radiata †leaf oil, Glyceryl linolenate, Grape seed oil, Helianthus annuus seed wax, Lemon oil †, Olive oil, Rosemary oil †, Safflower oil, Sunflower oil, Squalene, Tocopherol, Toxicodendron vernicifluum fruit rind wax.

Questions?

Questions? call 1-800-371-3515

PRINCIPAL DISPLAY PANEL - 50 g Tube

Thieves™ Essential Oil-Infused Chest Rub

Essential Oil-Infused

CHEST RUB

Cough suppresant

Topical Analgesic

Ointment

Maximum Strength

NET WT 1.76OZ (50g)